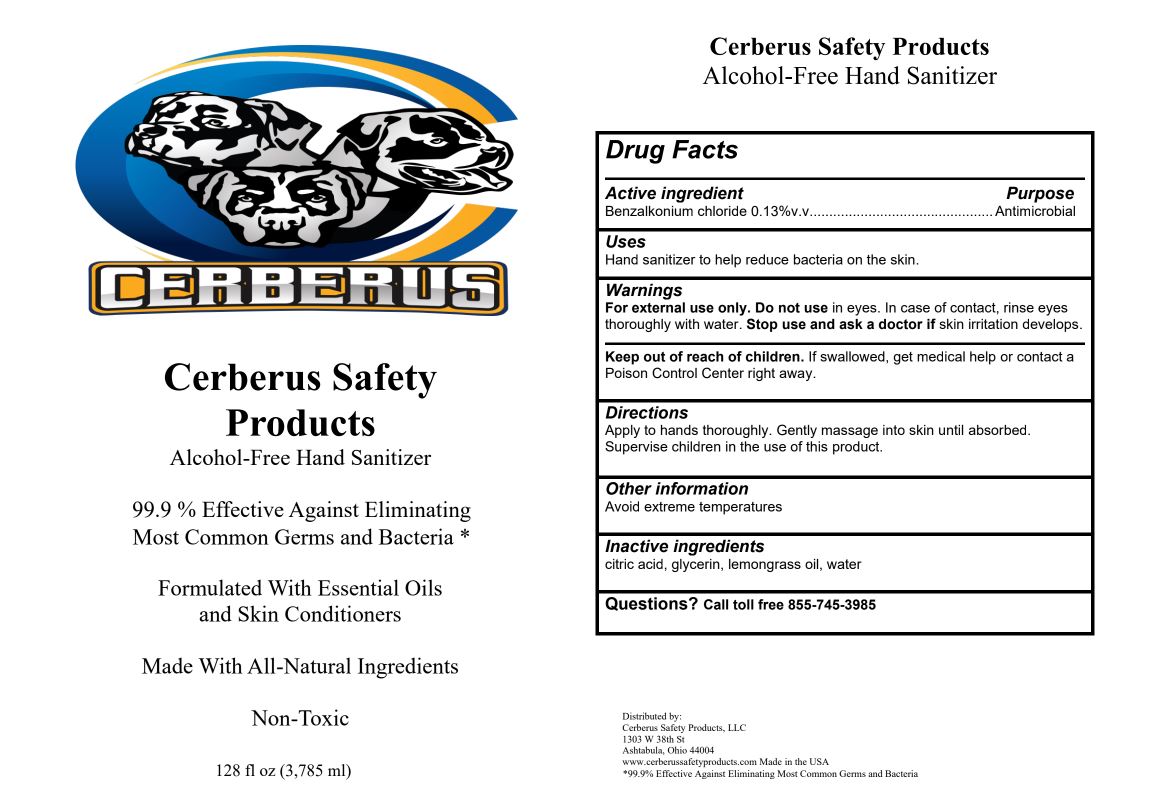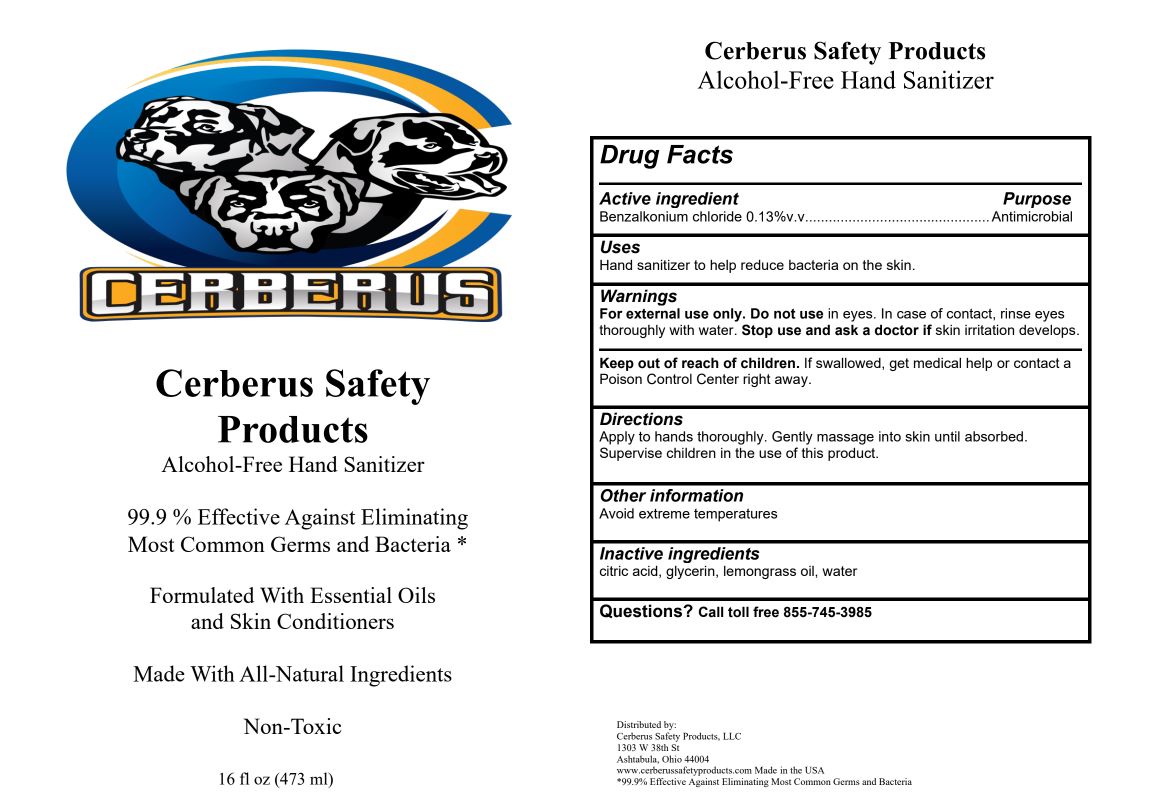 DRUG LABEL: Cerberus Alcohol-Free Hand Sanitizer
NDC: 80892-005 | Form: AEROSOL, FOAM
Manufacturer: GLOBAL CO PAK LLC
Category: otc | Type: HUMAN OTC DRUG LABEL
Date: 20201207

ACTIVE INGREDIENTS: BENZALKONIUM CHLORIDE 0.13 g/100 mL
INACTIVE INGREDIENTS: WEST INDIAN LEMONGRASS OIL; GLYCERIN; CITRIC ACID MONOHYDRATE; WATER

Active Ingredient(s)

Alcohol 0.13% v/v. Purpose: Antimicrobial

Purpose

Antimicrobial, Hand Sanitizer

Use

Hand Sanitizer to help reduce bacteria that potentially can cause disease. For use when soap and water are not available.

Warnings

For external use only. Do not use in eyes. In case of contact, rinse eyes thoroughly with water. Stop use and ask doctor if skin irritation develops.

Do not use

- in children less than 2 months of age
- on open skin wounds

When using this product keep out of eyes, ears, and mouth. In case of contact with eyes, rinse eyes thoroughly with water.
Stop use and ask a doctor if irritation or rash occurs. These may be signs of a serious condition.
Keep out of reach of children. If swallowed, get medical help or contact a Poison Control Center right away.

Stop use and ask a doctor if irritation or rash occurs. These may be signs of a serious condition.

Keep out of reach of children. If swallowed, get medical help or contact a Poison Control Center right away.

Directions

- Place enough product on hands to cover all surfaces. Rub hands together until dry.
- Supervise children under 6 years of age when using this product to avoid swallowing.

Other information

- Store between 15-30C (59-86F)
- Avoid freezing and excessive heat above 40C (104F)

Inactive ingredients

Citric acid, glycerin, lemongrass oil, water

Package Label - Principal Display Panel

473 mL NDC: 80892-005-16

3785 ml NDC: 80892-005-01